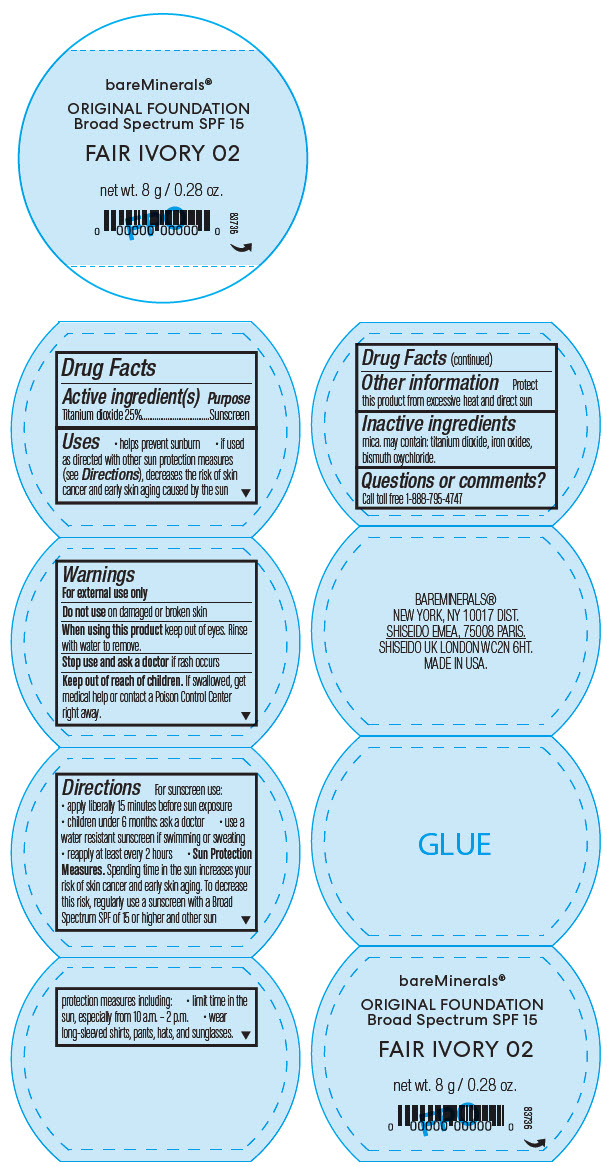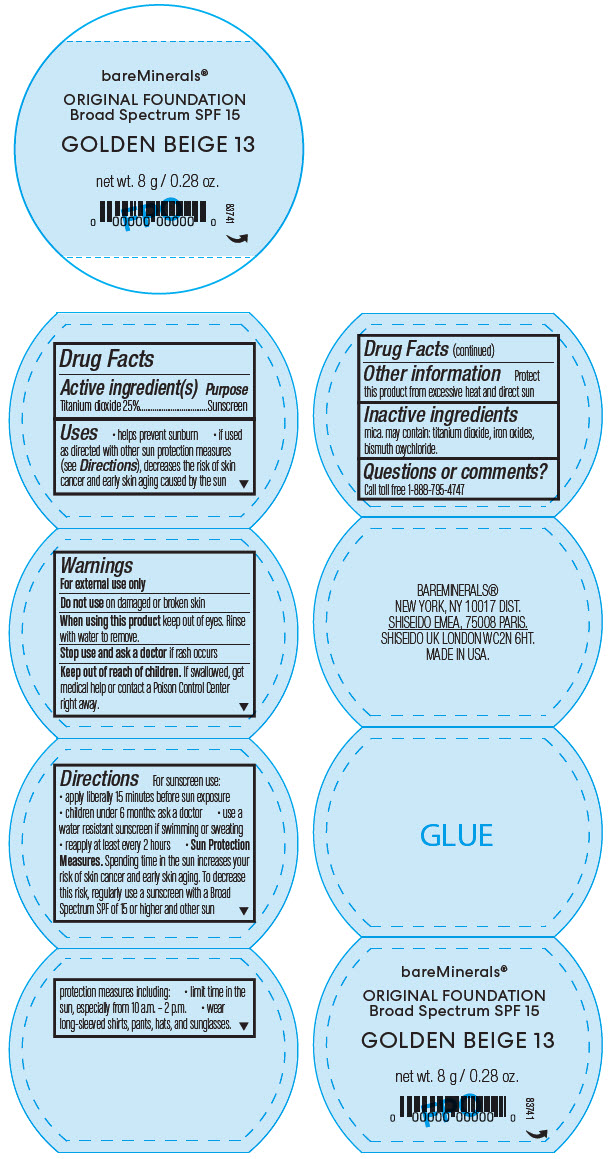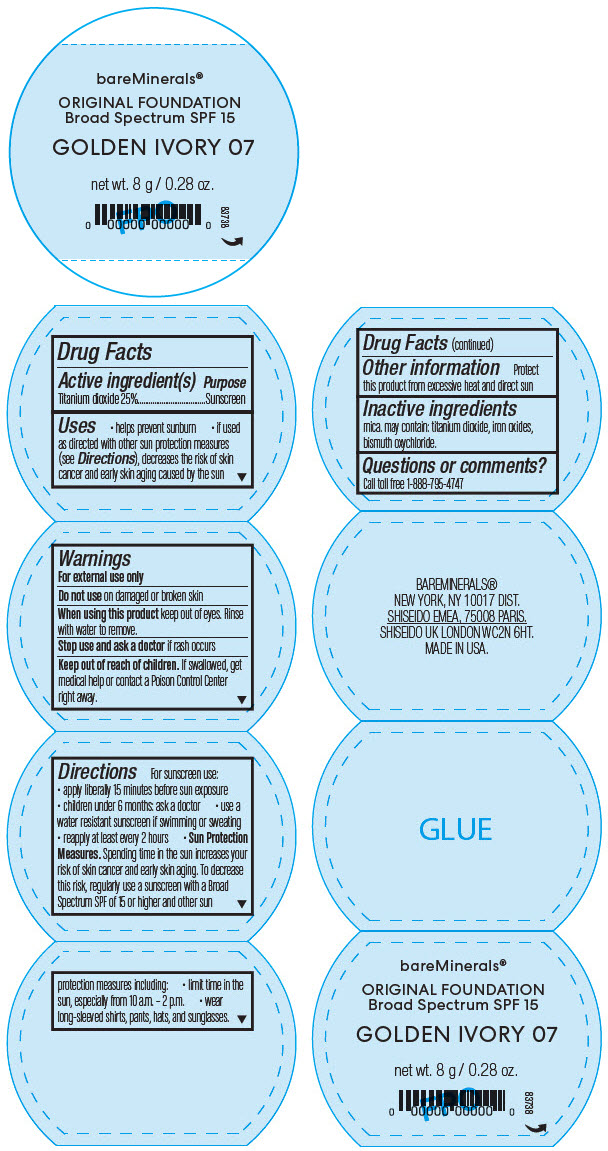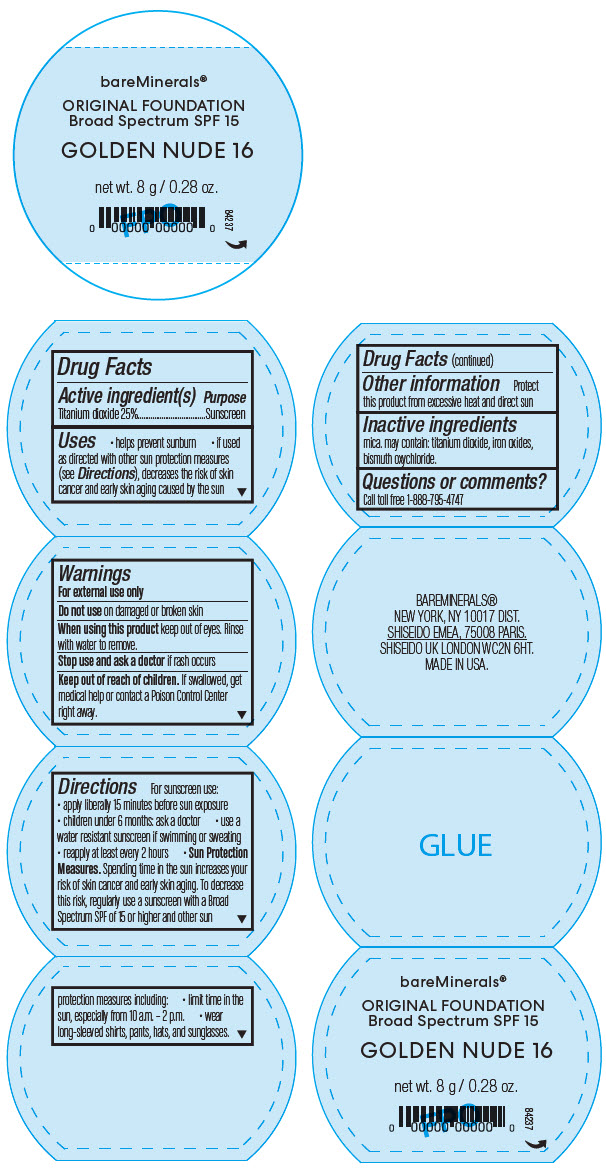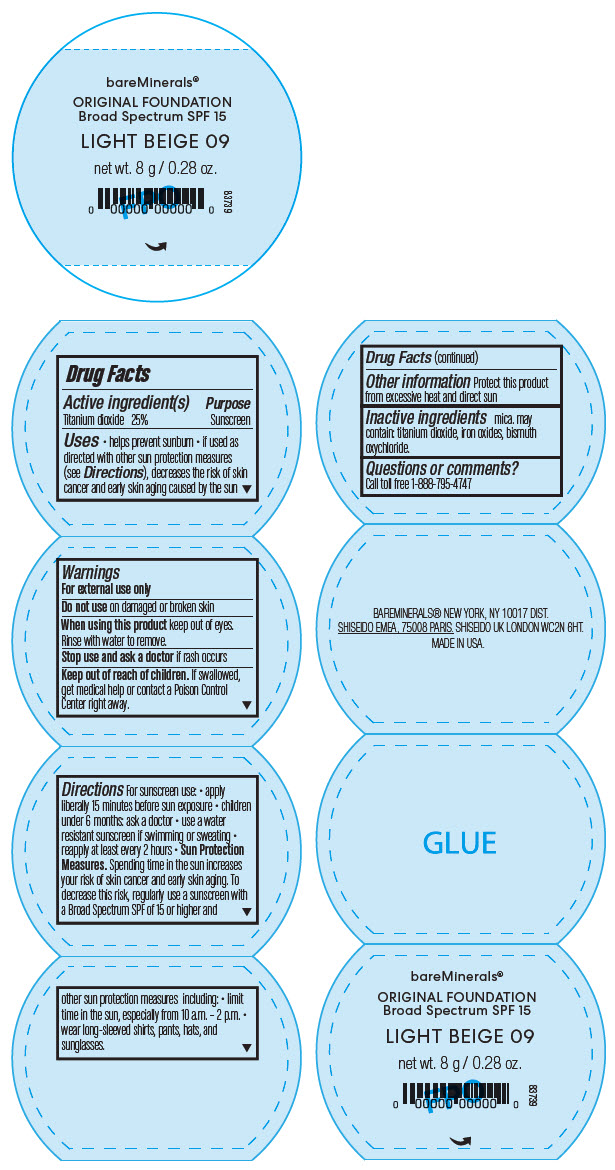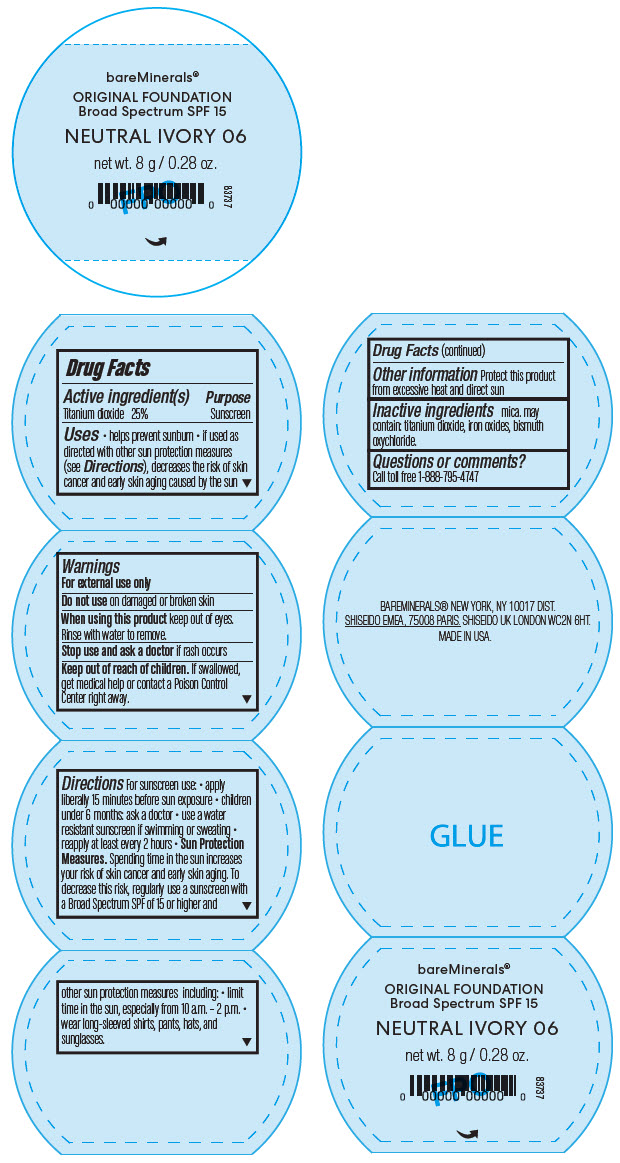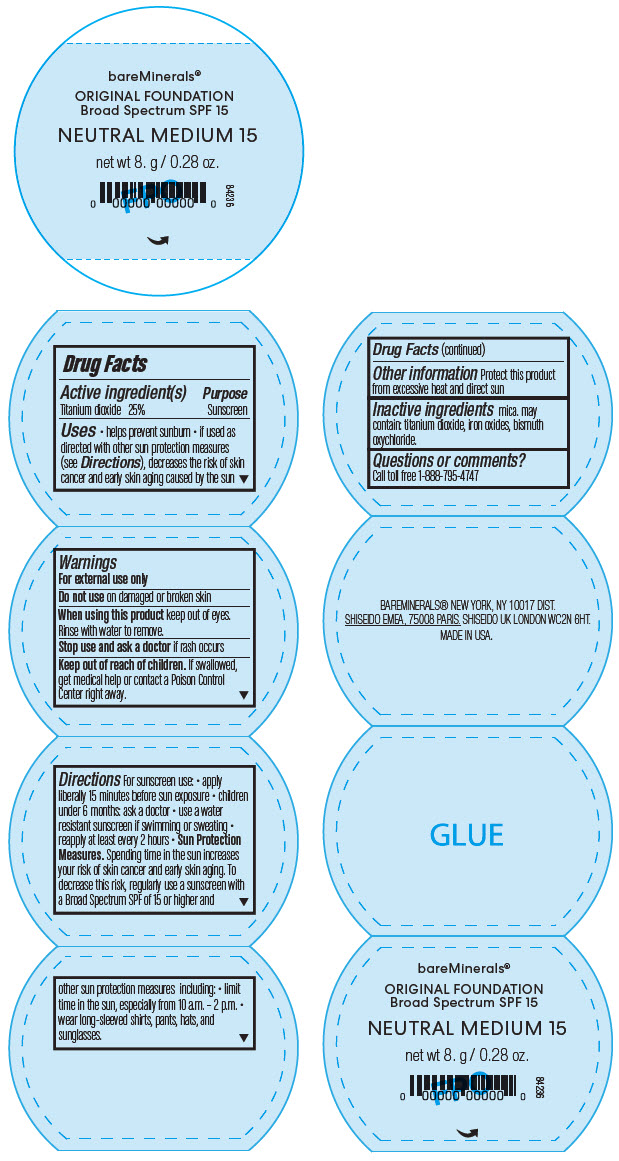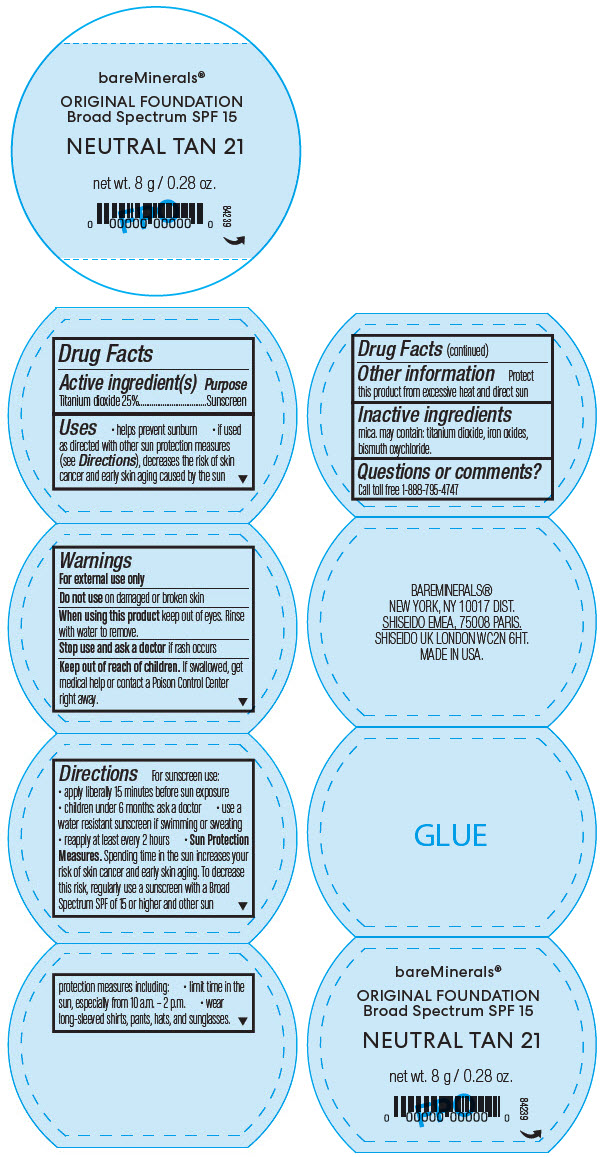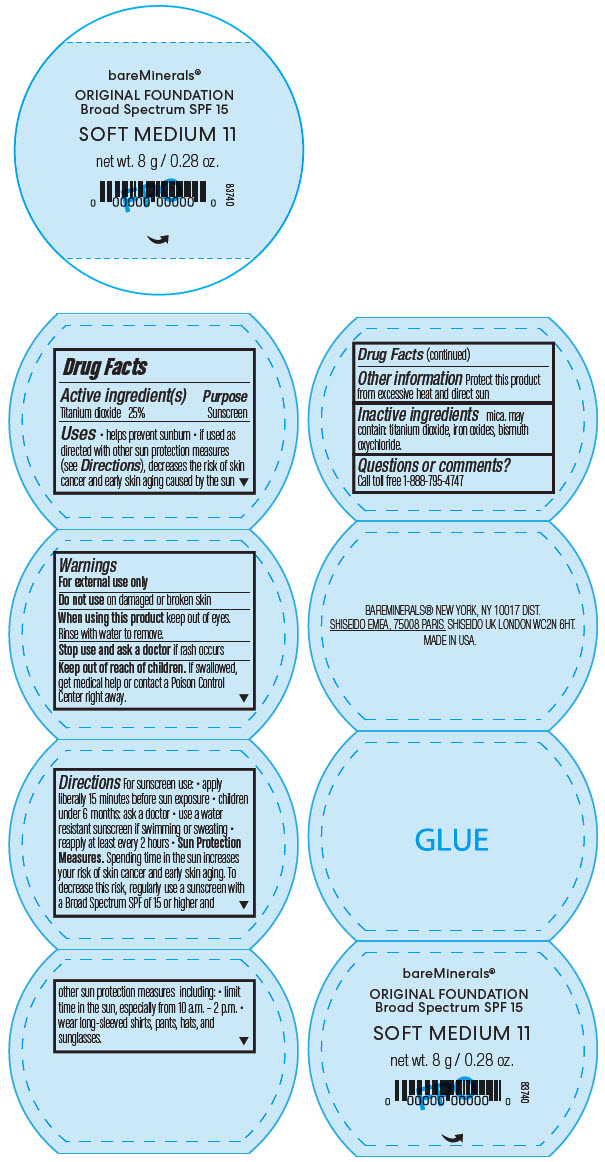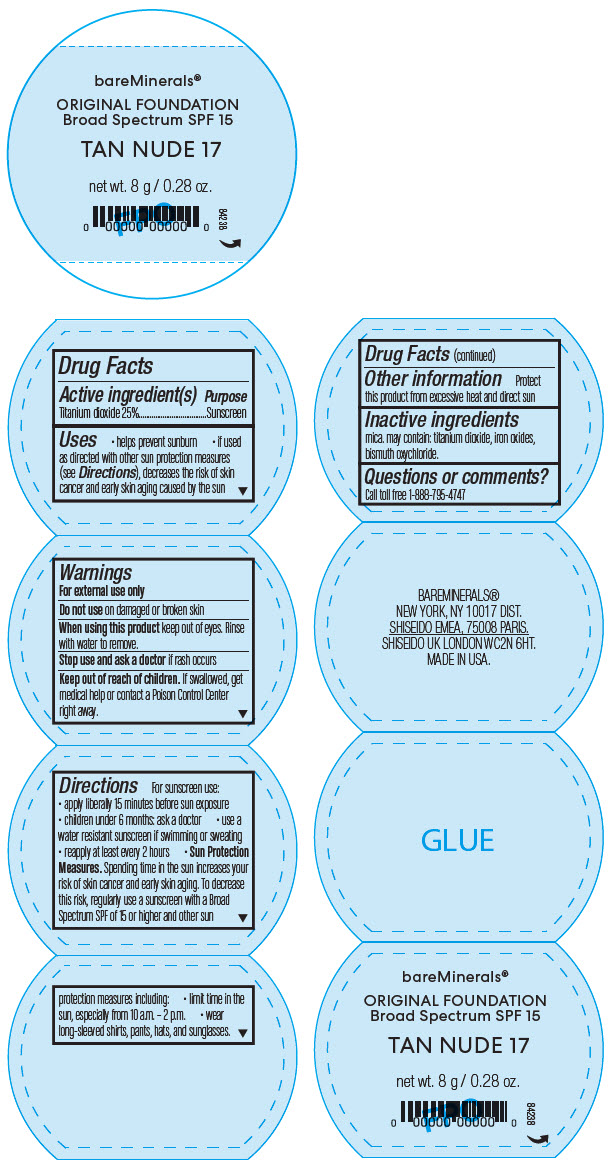 DRUG LABEL: bareMinerals Original Foundation Broad Spectrum SPF 15
NDC: 98132-899 | Form: POWDER
Manufacturer: Orveon Global US LLC
Category: otc | Type: HUMAN OTC DRUG LABEL
Date: 20231004

ACTIVE INGREDIENTS: TITANIUM DIOXIDE 25 g/100 g
INACTIVE INGREDIENTS: MICA; FERRIC OXIDE RED; BISMUTH OXYCHLORIDE

bareMinerals Original Foundation Broad Spectrum SPF 15

Drug Facts

Active ingredient(s)

Titanium dioxide 25%

Purpose

Sunscreen

Uses

- helps prevent sunburn
- if used as directed with other sun protection measures (see Directions), decreases the risk of skin cancer and early skin aging caused by the sun

Warnings

For external use only

Do not use on damaged or broken skin

When using this product keep out of eyes. Rinse with water to remove.

Stop use and ask a doctor if rash occurs

Keep out of reach of children. If product is swallowed, get medical help or contact a Poison Control Center right away.

Directions

For sunscreen use:

- apply liberally 15 minutes before sun exposure
- use a water resistant sunscreen if swimming or sweating
- reapply at least every 2 hours
- children under 6 months: ask a doctor
- Sun protection measures. Spending tirne in the sun increases your risk of skin cancer and early skin aging. To decrease this risk, regularly use a sunscreen with a Broad Spectrum SPF of 15 or higher and other sun protection measures including:
  - limit time in the sun, especially from 10 a.m. - 2 p.m.
  - wear long-sleeve shirts, pants, hats, and sunglasses

Inactive ingredients

mica. may contain: titanium dioxide, iron oxides, bismuth oxychloride.

Other information

Protect this product from excessive heat and direct sun

Questions or comments?

Call toll free 1-888-795-4747

Dist. by Bare Escentuals Beauty, Inc., San Francisco, CA 94105 USA

PRINCIPAL DISPLAY PANEL - 2 g Jar Label - Fair Ivory

bareMinerals®

ORIGINAL FOUNDATION
Broad Spectrum SPF 15

FAIR IVORY 02

net wt. 8 g / 0.28 oz.

83736

PRINCIPAL DISPLAY PANEL - 2 g Jar Label - Golden Beige

bareMinerals®

ORIGINAL FOUNDATION
Broad Spectrum SPF 15

GOLDEN BEIGE 13

net wt. 8 g / 0.28 oz.

83741

PRINCIPAL DISPLAY PANEL - 2 g Jar Label - Golden Ivory

bareMinerals®

ORIGINAL FOUNDATION
Broad Spectrum SPF 15

GOLDEN IVORY 07

net wt. 8 g / 0.28 oz.

83738

PRINCIPAL DISPLAY PANEL - 2 g Jar Label - Golden Nude

bareMinerals®

ORIGINAL FOUNDATION
Broad Spectrum SPF 15

GOLDEN NUDE 16

net wt. 8 g / 0.28 oz.

84237

PRINCIPAL DISPLAY PANEL - 2 g Jar Label - Light Beige

bareMinerals®

ORIGINAL FOUNDATION
Broad Spectrum SPF 15

LIGHT BEIGE 09

net wt. 8 g / 0.28 oz.

83739

PRINCIPAL DISPLAY PANEL - 2 g Jar Label - Neutral Ivory

bareMinerals®

ORIGINAL FOUNDATION
Broad Spectrum SPF 15

NEUTRAL IVORY 06

net wt. 8 g / 0.28 oz.

83737

PRINCIPAL DISPLAY PANEL - 2 g Jar Label - Neutral Medium

bareMinerals®

ORIGINAL FOUNDATION
Broad Spectrum SPF 15

NEUTRAL MEDIUM 15

net wt. 8 g / 0.28 oz.

84236

PRINCIPAL DISPLAY PANEL - 2 g Jar Label - Neutral Tan

bareMinerals®

ORIGINAL FOUNDATION
Broad Spectrum SPF 15

NEUTRAL TAN 21

net wt. 8 g / 0.28 oz.

84239

PRINCIPAL DISPLAY PANEL - 2 g Jar Label - Soft Medium

bareMinerals®

ORIGINAL FOUNDATION
Broad Spectrum SPF 15

SOFT MEDIUM 11

net wt. 8 g / 0.28 oz.

83740

PRINCIPAL DISPLAY PANEL - 2 g Jar Label - Tan Nude

bareMinerals®

ORIGINAL FOUNDATION
Broad Spectrum SPF 15

TAN NUDE 17

net wt. 8 g / 0.28 oz.

84238